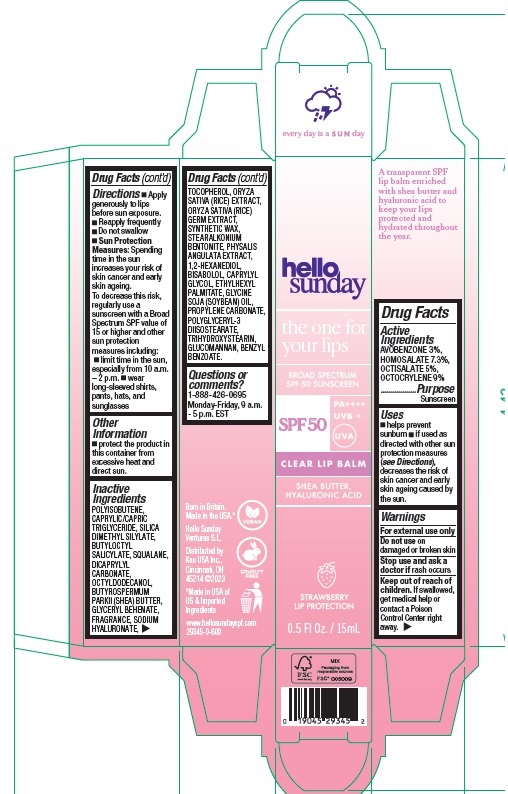 DRUG LABEL: Hello Sunday The One For Your Lips Clear Lip Balm SPF 50
NDC: 10596-806 | Form: STICK
Manufacturer: Kao USA Inc.
Category: otc | Type: HUMAN OTC DRUG LABEL
Date: 20251117

ACTIVE INGREDIENTS: OCTISALATE 50 mg/1 mL; AVOBENZONE 30 mg/1 mL; OCTOCRYLENE 90 mg/1 mL; HOMOSALATE 73 mg/1 mL
INACTIVE INGREDIENTS: POLYISOBUTYLENE (1300 MW); HYALURONATE SODIUM; RICE GERM; SILICON DIOXIDE; TRIHYDROXYSTEARIN; SILICA DIMETHYL SILYLATE; SQUALANE; DICAPRYLYL CARBONATE; BUTYLOCTYL SALICYLATE; OCTYLDODECANOL; SHEA BUTTER; TOCOPHEROL; GLYCERYL MONOBEHENATE; SYNTHETIC WAX (1200 MW); 1,2-HEXANEDIOL; PROPYLENE CARBONATE; ETHYLHEXYL PALMITATE; LEVOMENOL; KONJAC MANNAN; PHYSALIS ANGULATA WHOLE; CAPRYLYL GLYCOL; BENZYL BENZOATE; POLYGLYCERYL-3 DIISOSTEARATE; MEDIUM-CHAIN TRIGLYCERIDES; SOYBEAN OIL

Hello Sunday The One For Your Lips Clear Lip Balm SPF 50

Active Ingredients

AVOBENZONE 3%
HOMOSALATE 7.3%
OCTISALATE 5%
OCTOCRYLENE 9%

Purpose

Sunscreen

Uses

- helps prevent sunburn
- if used as directed with other sun protection measures (see Directions), decreases the risk of skin cancer and early skin ageing caused by the sun.

Warnings

For external use only

Do not use

on damaged or broken skin

Stop use and ask a doctor if

rash occurs

Keep out of reach of children.

If swallowed, get medical help or contact a Poison Control Center right away.

Directions

- Apply generously to lips before sun exposure.
- Reapply frequently
- Do not swallow
- Sun Protection Measures: Spending time in the sun increases your risk of skin cancer and early skin ageing. To decrease this risk, regularly use a sunscreen with a Broad Spectrum SPF value of 15 or higher and other sun protection measures including:
- limit time in the sun, especially from 10 a.m. – 2 p.m.
- wear long-sleeved shirts, pants, hats, and sunglasses

Other Information

- protect the product in this container from excessive heat and direct sun.

Inactive Ingredients

POLYISOBUTENE, CAPRYLIC/CAPRIC TRIGLYCERIDE, SILICA DIMETHYL SILYLATE, BUTYLOCTYL SALICYLATE, SQUALANE, DICAPRYLYL CARBONATE, OCTYLDODECANOL, BUTYROSPERMUM PARKII (SHEA) BUTTER, GLYCERYL BEHENATE, FRAGRANCE, SODIUM HYALURONATE, TOCOPHEROL, ORYZA SATIVA (RICE) EXTRACT, ORYZA SATIVA (RICE) GERM EXTRACT, SYNTHETIC WAX, STEARALKONIUM BENTONITE, PHYSALIS ANGULATA EXTRACT, 1,2-HEXANEDIOL, BISABOLOL, CAPRYLYL GLYCOL, ETHYLHEXYL PALMITATE, GLYCINE SOJA (SOYBEAN) OIL, PROPYLENE CARBONATE, POLYGLYCERYL-3 DIISOSTEARATE, TRIHYDROXYSTEARIN, GLUCOMANNAN, BENZYL BENZOATE.

Questions or comments?

1-888-426-0695
Monday-Friday, 9 a.m. - 5 p.m. EST